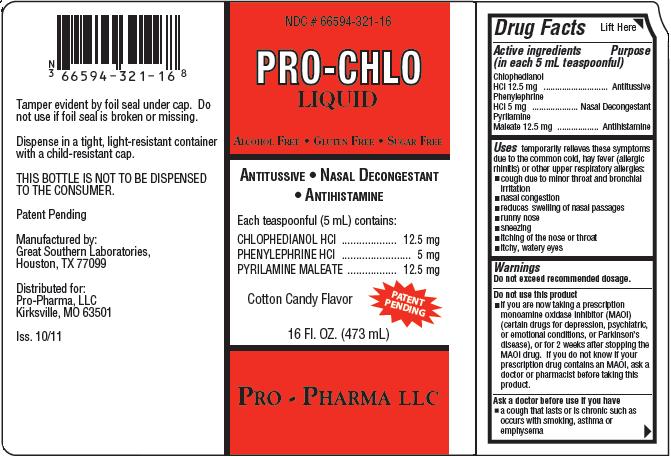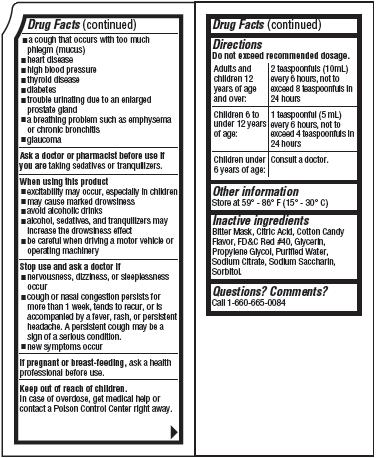 DRUG LABEL: PRO-CHLO
NDC: 66594-321 | Form: LIQUID
Manufacturer: Pro-Pharma, LLC
Category: otc | Type: HUMAN OTC DRUG LABEL
Date: 20111116

ACTIVE INGREDIENTS: Chlophedianol Hydrochloride 12.5 mg/5 mL; Phenylephrine Hydrochloride 5 mg/5 mL; Pyrilamine Maleate 12.5 mg/5 mL
INACTIVE INGREDIENTS: Citric Acid Monohydrate; Glycerin; Propylene Glycol; Water; Sodium Citrate; Saccharin Sodium; Sorbitol

PRO-CHLO LIQUID

Drug Facts

Active ingredients
(in each 5 mL teaspoonful)
Chlophedianol HCl 12.5 mg
Phenylephrine HCl 5 mg
Pyrilamine Maleate 12.5 mg

Purpose

Antitussive
Nasal Decongestant
Antihistamine

Uses

temporarily relieves these symptoms due to the common cold, hay fever (allergic rhinitis) or other upper respiratory allergies:

- cough due to minor throat and bronchial irritation
- nasal congestion
- reduces swelling of nasal passages
- runny nose
- sneezing
- itching of the nose or throat
- itchy, water eyes

Warnings

Do not exceed recommended dosage.

Do not use this product

- if you are now taking a prescription monoamine oxidase inhibibor (MAOI) (certain drugs for depression, psychiatric, or emotional conditions, or Parkinson's disease), or for 2 weeks after stopping the MAOI drug. If you do not know if your prescription drug contains an MAOI, ask a doctor or pharmacist before taking this product.

Ask a doctor before use if you have

- a cough that lasts or is chronic such as occurs with smoking, asthma, or emphysema
- a cough that occurs with too much phlegm (mucus)
- heart disease
- high blood pressure
- thyroid disease
- diabetes
- trouble urinating due to an enlarged prostate gland
- a breathing problem such as emphysema or chronic bronchitis
- glaucoma

Ask a doctor or pharmacist before use if you are taking sedatives or tranquilizers.

When using this product

- excitability may occur, especially in children
- may cause marked drowsiness
- avoid alcoholic drinks
- alcohol, sedatives, and tranquilizers may increase the drowsiness effect
- be careful when driving a motor vehicle or operating machinery

Stop use and ask a doctor if

- nervousness, dizziness, or sleeplessness occur
- cough or nasal congestion persists for more than 1 week, tends to recur, or is accompanied by a fever, rash, or persistent headache. A persistent cough may be a sign of a serious condition.
- new symptoms occur

PREGNANCY OR BREAST FEEDING

If pregnant or breast-feeding, ask a health professional before use.

Keep out of reach of children.

In case of overdose, get medical help or contact a Poison Control Center right away.

Directions

Do not exceed recommended dosage.

Adults and children 12 years of age and over: | 2 teaspoonfuls (10 mL) every 6 hours, not to exceed 8 teaspoonfuls in 24 hours
Children 6 to under 12 years of age: | 1 teaspoonful (5 mL) every 6 hours, not to exceed 4 teaspoonfuls in 24 hours
Children under 6 years of age: | Consult a doctor.

Other information

Store at 59°-86°F (15°-30°C)

Inactive ingredients

Bitter Mask, Citric Acid, Cotton Candy Flavor, FD&C Red #40, Glycerin, Propylene Glycol, Purified Water, Sodium Citrate, Sodium Saccharin, Sorbitol.

Questions? Comments?

Call 1-660-665-0084

Product Packaging

The packaging below represents the labeling currently used:
Principal display panel and side panel for 473 mL label:
NDC #66594-321-16
PRO-CHLO
LIQUID
ALCOHOL FREE·GLUTEN FREE·SUGAR FREE
ANTITUSSIVE · NASAL DECONGESTANT
· ANTIHISTAMINE
Each teaspoonful (5 mL) contains:
CHLOPHEDIANOL HCL...............................12.5 mg
PHENYLEPHRINE HCL....................................5 mg
PYRILAMINE MALEATE..............................12.5 mg
Cotton Candy Flavor
PATENT PENDING
16 FL. OZ. (473 mL)
PRO-PHARMA LLC
Tamper evident by foil seal under cap. Do not use if foil
seal is broken or missing.
Dispense in a tight, light-resistant container with a child-resistant
cap.
THIS BOTTLE IS NOT TO BE DISPENSED TO THE CONSUMER.
Patent Pending
Manufactured by:
Great Southern Laboratories,
Houstin, TX 77099
Distributed for:
Pro-Pharma, LLC
Kirksville, MO 63501
Iss. 10/11